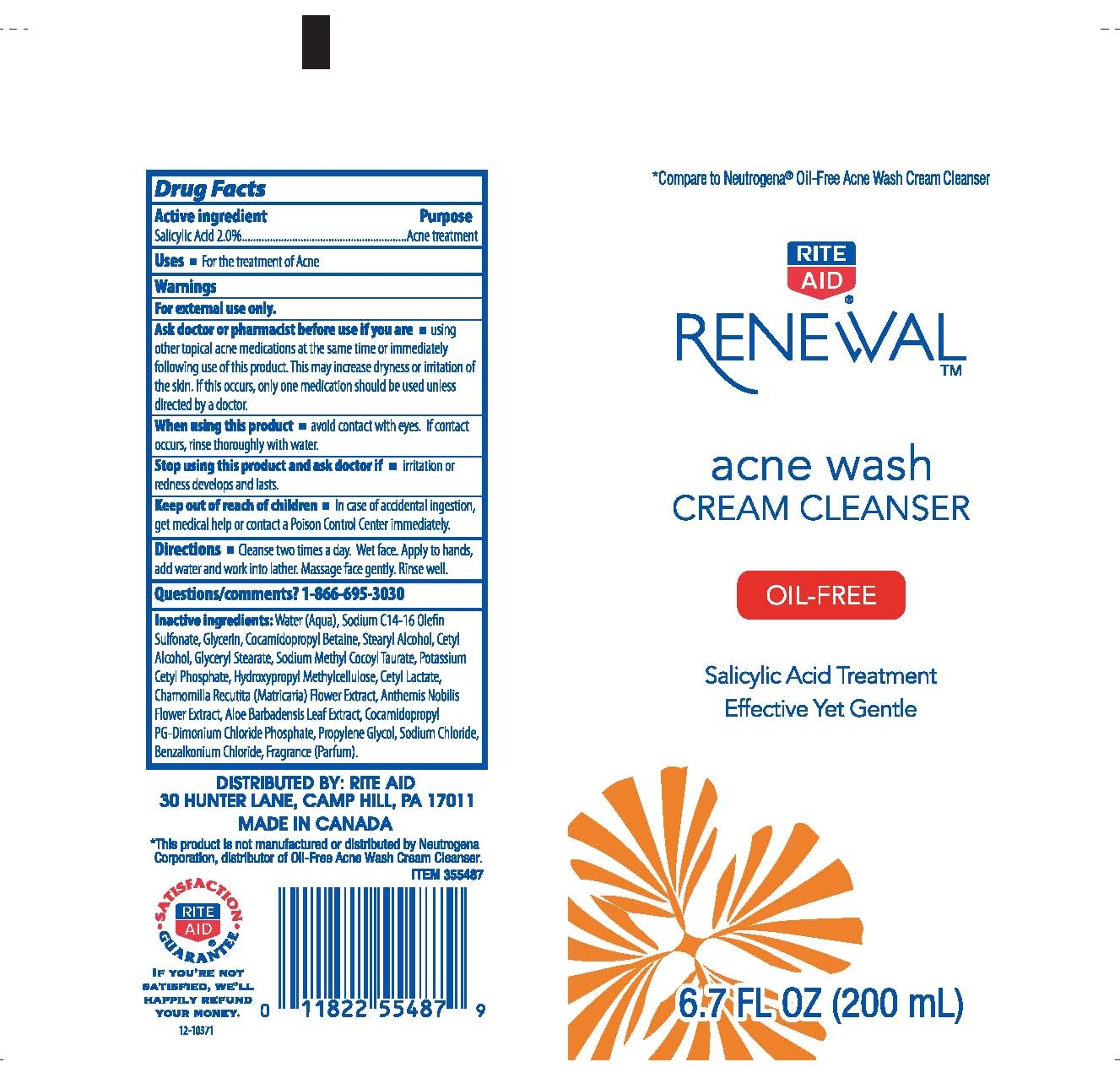 DRUG LABEL: RENEWAL 
NDC: 11822-8200 | Form: CREAM
Manufacturer: RITE AID CORPORATION
Category: otc | Type: HUMAN OTC DRUG LABEL
Date: 20110728

ACTIVE INGREDIENTS: SALICYLIC ACID 2 mL/100 mL
INACTIVE INGREDIENTS: WATER; SODIUM C14 OLEFIN SULFONATE; GLYCERIN; COCAMIDOPROPYL BETAINE; STEARYL ALCOHOL; CETYL ALCOHOL; GLYCERYL MONOSTEARATE; SODIUM METHYL COCOYL TAURATE; POTASSIUM CETYL PHOSPHATE; HYPROMELLOSES; CHAMOMILE; CHAMAEMELUM NOBILE FLOWER; ALOE VERA LEAF; COCAMIDOPROPYL PG-DIMONIUM CHLORIDE PHOSPHATE; PROPYLENE GLYCOL; SODIUM CHLORIDE; BENZALKONIUM CHLORIDE

DRUG FACTS

ACTIVE INGREDIENT

SALICYLIC ACID 2.0%

PURPOSE

ACNE TREATMENT

USES

WARNINGS

FOR EXTERNAL USE ONLY.

ASK DOCTOR OR PHARMACIST BEFORE USE IF YOU ARE

USING OTHER TOPICAL ACNE MEDICATIONS AT THE SAME TIME OR IMMEDIATELY FOLLOWING USE OF THIS PRODUCT. THIS MAY INCREASE DRYNESS OR IRRITATION OF THE SKIN. IF THIS OCCURS, ONLY ONE MEDICATION SHOULD BE USED UNLESS DIRECTED BY A DOCTOR.

WHEN USING THIS PRODUCT

AVOID CONTACT WITH EYES. IF CONTACT OCCURS, RINSE THOROUGHLY WITH WATER.

STOP USING THIS PRODUCT AND ASK DOCTOR IF

IRRITATION OR REDNESS DEVELOPS AND LASTS.

KEEP OUT OF REACH OF CHILDREN

IN CASE OF ACCIDENTAL INGESTION, GET MEDICAL HELP OR CONTACT A POISON CONTROL CENTER IMMEDIATELY.

DIRECTIONS

CLEANSE TWO TIMES A DAY. WET FACE. APPLY TO HANDS, ADD WATER AND WORK INTO LATHER. MASSAGE FACE GENTLY. RINSE WELL.

QUESTIONS/COMMENTS?

1-866-695-3030

INACTIVE INGREDIENTS

WATER, SODIUM C14-16 OLEFIN SULFONATE, GLYCERIN, COCAMIDOPROPYL BETAINE, STEARYL ALCOHOL, CETYL ALCOHOL, GLYCERYL STEARATE, SODIUM METHYL COCOYL TAURATE, POTASSIUM CETYL PHOSPHATE, HYDROXYPROPYL METHYLCELLULOSE, CETYL LACTATE, CHAMOMILLA RECUTITA (MATRICARIA) FLOWER EXTRACT, ANTHEMIS NOBILIS FLOWER EXTRACT, ALOE BARBADENSIS LEAF EXTRACT, COCAMIDOPROPYL PG-DIMONIUM CHLORIDE PHOSPHATE, PROPYLENE GLYCOL, SODIUM CHLORIDE, BENZALKONIUM CHLORIDE, FRAGRANCE.